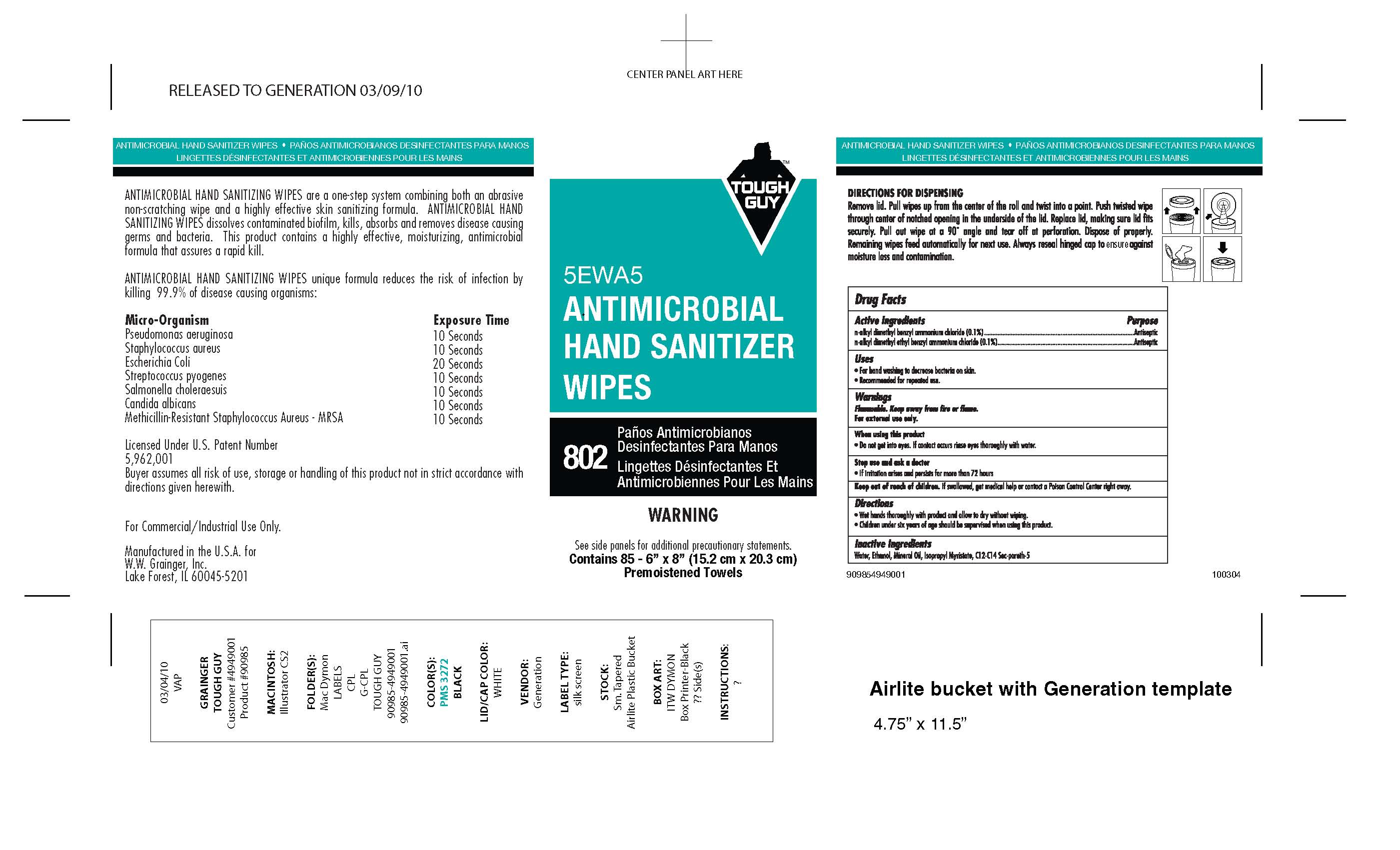 DRUG LABEL: Tough Guy Hand Sanitizer Wipes
NDC: 40096-0802 | Form: CLOTH
Manufacturer: W.W. Grainger, Inc.
Category: otc | Type: HUMAN OTC DRUG LABEL
Date: 20100317

ACTIVE INGREDIENTS: BENZALKONIUM CHLORIDE 0.1 g/970 mL; BENZETHONIUM CHLORIDE 0.1 g/970 mL
INACTIVE INGREDIENTS: Alcohol 20.0 g/970 mL; WATER 78.1 g/970 mL; ISOPROPYL MYRISTATE 0.3 g/970 mL; MINERAL OIL 0.7 g/970 mL

Active Ingredient Purpose

n-alkyl dimethyl benzyl ammonium chloride (0.1%)................................................Antiseptic

n-alkyl dimethyl ethyl benzyl ammonium chloride (0.1%)......................................Antiseptic

Uses

- For hand washing to decrease bacteria on skin.
- Recommended for repeated use.

Warnings

Flammable, keep away from heat and flame.

For external use only.

When using this product

- do not get into eyes. If contact occurs rinse eyes thoroughly with water.

Stop use and ask a doctor

- If irritation arises and persists for more than 72 hours.

Keep out of reach of children. If swallowed, get medical help or contact a Poison Control Center right away.

Directions

- Wet hands thoroughly with product and allow to dry without wiping.
- Children under six years of age should be supervised when using this product.

QUESTIONS

Inactive Ingredients

Water, Ethanol, Mineral Oil, Isopropyl Myristate, C12-C14 Sec-pareth-5